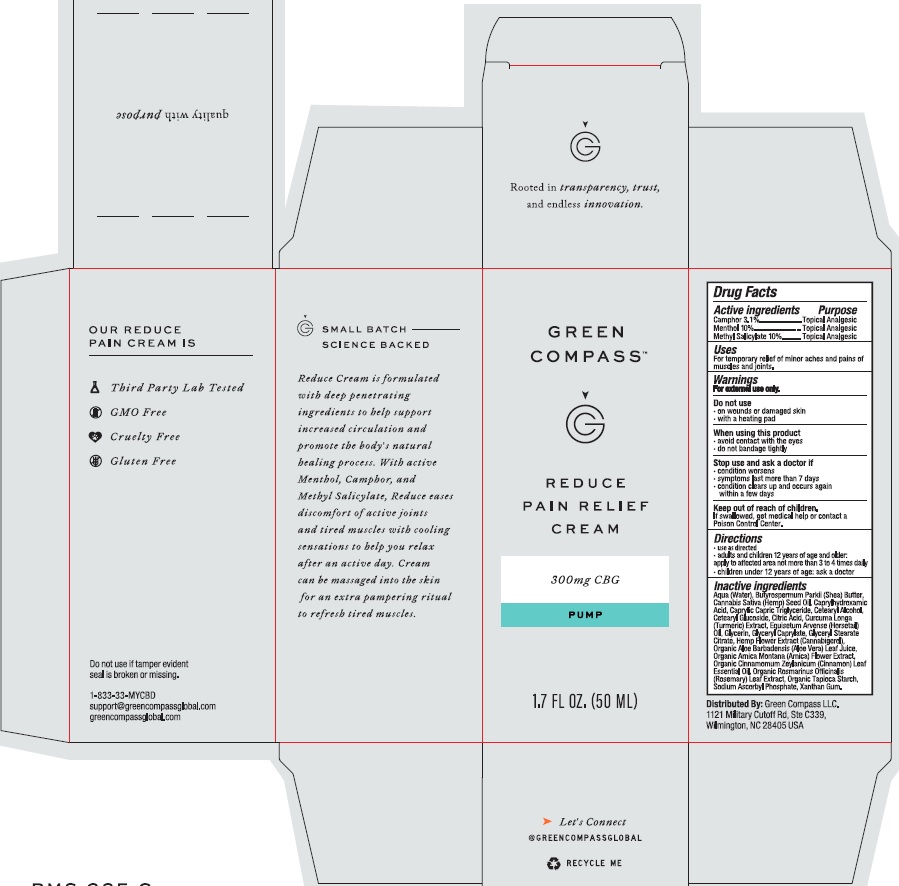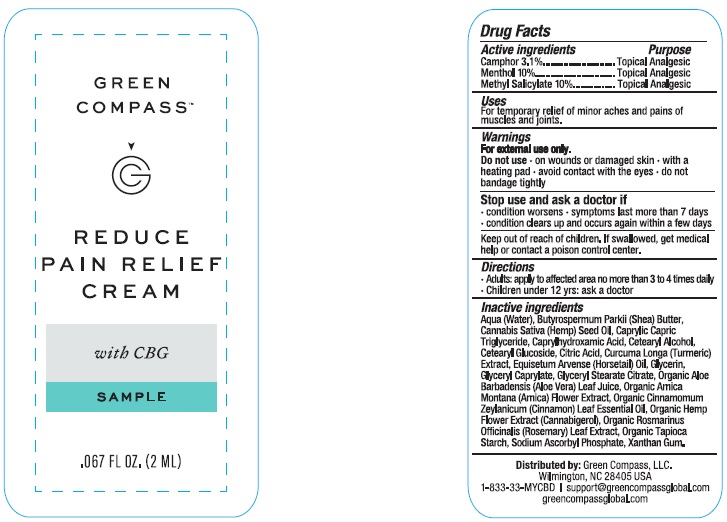 DRUG LABEL: Green Compass Reduce Pain Relief
NDC: 73132-004 | Form: CREAM
Manufacturer: Green Compass, Inc.
Category: otc | Type: HUMAN OTC DRUG LABEL
Date: 20250101

ACTIVE INGREDIENTS: CAMPHOR (NATURAL) 3.1 g/100 mL; MENTHOL 10 g/100 mL; METHYL SALICYLATE 10 g/100 mL
INACTIVE INGREDIENTS: XANTHAN GUM; ARNICA MONTANA; CANNABIGEROL; GLYCERYL STEARATE CITRATE; CINNAMON LEAF OIL; EQUISETUM ARVENSE WHOLE; TURMERIC; MEDIUM-CHAIN TRIGLYCERIDES; HEMP; CETOSTEARYL ALCOHOL; CETEARYL GLUCOSIDE; CITRIC ACID MONOHYDRATE; GLYCERIN; GLYCERYL CAPRYLATE; SHEA BUTTER; CAPRYLHYDROXAMIC ACID; ALOE VERA LEAF; ROSEMARY; STARCH, TAPIOCA; SODIUM ASCORBYL PHOSPHATE; WATER

Green Compass Reduce Pain Relief Cream

Drug Facts

Active ingredients

Camphor 3.1%

Menthol 10%

Methyl Salicylate 10%

Purpose

Topical Analgesic

Topical Analgesic

Topical Analgesic

Uses

For temporary relief of minor aches and pains of muscles and joints.

Warnings

For external use only.

Do not use

- on wounds or damaged skin
- with a heating pad

When using this product

- avoid contact with the eyes
- do not bandage tightly

Stop use and ask a doctor if

- condition worsens
- symptoms last more than 7 days
- condition clears up and occurs again within a few days

Keep out of reach of children. If swallowed, get medical help or contact a Poison Control Center.

Directions

- use as directed
- adults and children 12 years of age and older: apply to affected area not more than 3 to 4 times daily
- children under 12 years of age: ask a doctor

Inactive ingredients

Aqua (water), butyrospermum parkii (shea) butter, cannabis sativa (hemp) seed oil, caprylhydroxamid acid, caprylic capric triglyceride, cetearyl alcohol, cetearyl glucoside, citric acid, curcuma longa (turmeric) extract, equisetum arvense (horsetail) oil, glycerin, glyceryl caprylate, glyceryl stearate citrate, hemp flower extract (cannabigerol), organic aloe barbadensis (aloe vera) leaf juice, organic arnica montana (arnica) flower extract, organic cinnamomum zeylanicum (cinnamon) leaf essential oil, organic rosmarinus officinalis (rosemary) leaf extract, organic tapioca starch, sodium ascorbyl phosphate, xanthan gum.

Distributed by:

Green Compass LLC.

1121 Military Cutoff Rd., Ste C339

Wilmington, NC 28405 USA

Do not use if tamper evident seal is broken or missing.

1-833-33-MYCBD

support@greencompassglobal.com

greencompassglobal.com

PACKAGE LABEL

GREEN COMPASS

REDUCE

PAIN RELIEF

CREAM

300 mg CBG

PUMP

1.7 FL OZ (50 mL)